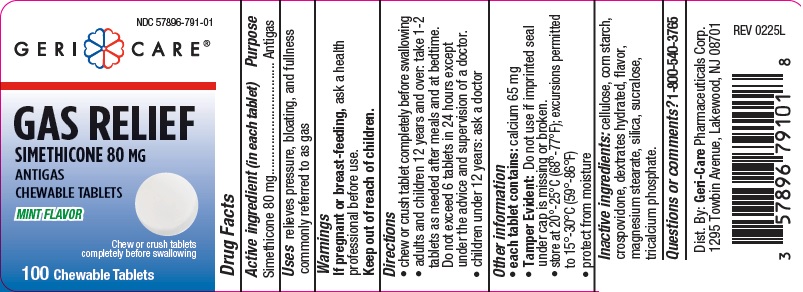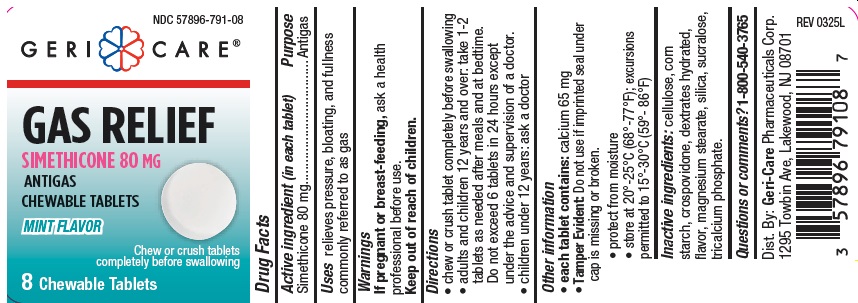 DRUG LABEL: SIMETHICONE
NDC: 57896-791 | Form: TABLET, CHEWABLE
Manufacturer: Geri-Care Pharmaceuticals, Corp
Category: otc | Type: HUMAN OTC DRUG LABEL
Date: 20251117

ACTIVE INGREDIENTS: DIMETHICONE 80 mg/1 1
INACTIVE INGREDIENTS: CELLULOSE, MICROCRYSTALLINE; DEXTRATES; SILICON DIOXIDE; TRICALCIUM PHOSPHATE; SUCRALOSE; STARCH, CORN; CROSPOVIDONE; MAGNESIUM STEARATE

gc 791

Active ingredient (in each tablet)

Simethicone 80 mg

Purpose

antigas

Uses

relieves pressure, bloating, and fullness
commonly referred to as gas

Warnings

If pregnant or breast feeding, ask a health professional before use.

Keep out of reach of children.

Directions

- chew or crush tablet completely before swallowing
- adults and children 12 years and over: take 1-2 tablets as needed after meals and at bedtime.

Do not exceed 6 tablets in 24 hours except under the advice and supervision of a doctor.

- children under 12 years: ask a doctor

Other information

- each tablet contains: calcium 65 mg
- Tamper Evident: Do not use if imprinted seal under cap is missing or broken
- store at 20°-25°C (68°-77°F); excursions permitted to 15°-30°C (59°-86°F)
- protect from moisture

Inactive ingredients

cellulose, corn starch, crospovidone, dextrates hydrated, flavor,
magnesium stearate, silica, sucralose, tricalcium phosphate.

Questions or comments?

1-800-540-3765